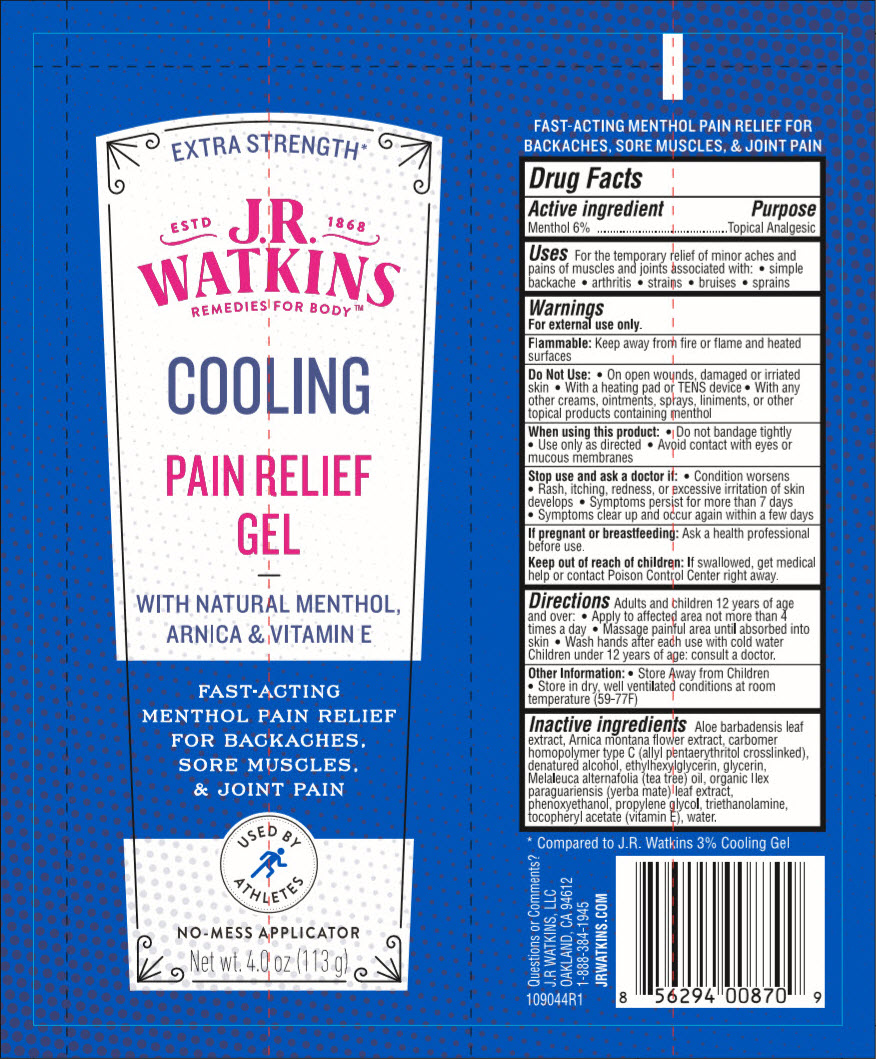 DRUG LABEL: Pain Relief
NDC: 72342-110 | Form: GEL
Manufacturer: J.R. Watkins, LLC.
Category: otc | Type: HUMAN OTC DRUG LABEL
Date: 20240320

ACTIVE INGREDIENTS: MENTHOL, UNSPECIFIED FORM 6 g/100 g
INACTIVE INGREDIENTS: ALOE VERA LEAF; ARNICA MONTANA FLOWER; CARBOMER HOMOPOLYMER TYPE C (ALLYL PENTAERYTHRITOL CROSSLINKED); ALCOHOL; ETHYLHEXYLGLYCERIN; GLYCERIN; TEA TREE OIL; ILEX PARAGUARIENSIS LEAF; PHENOXYETHANOL; PROPYLENE GLYCOL; TROLAMINE; .ALPHA.-TOCOPHEROL ACETATE; WATER

Pain Relief Gel
Extra Strength, Cooling

Drug Facts

Active Ingredient

Menthol 6%

Purpose

Topical Analgesic

Uses

For the temporary relief of minor aches and pains of muscles and joints associated with

- simple backache
- arthritis
- strains
- bruises
- sprains

Warnings

For external use only.

Flammable:Keep away from fire or flame and heated surfaces.

Do not use

- On open wounds, damaged or irritated skin
- With a heading pad or TENS device
- With any other creams, ointments, sprays, liniments, or other topical products containing menthol

When using this product

- Do not bandage tightly
- Use only as directed
- Avoid contact with eyes or mucous membranes

Stop use and ask a doctor if

- Condition worsens
- Rash, itching, redness, or excessive irritation of skin develops
- Symptoms persist for more than 7 days
- Symptoms clear up and occur again within a few days

If pregnant or breastfeeding

Ask a health professional before use.

Keep out of reach of children. If swallowed, get medical help or contact a Poison Control Center right away.

Directions

- Adults and children 12 years of age and older:
- Apply to affected area not more 4 times a day
- Massage painful area until absorbed into skin
- Wash hands after each use with cold water
- Children under 12 years of age: consult a doctor.

Other information

- Store away from children
- Store in dry, well-ventilated conditions at room temperature (59-77°F)

Inactive ingredients

Aloe barbadensis leaf extract, Arnica montana flower extract, carbomer homopolymer type C (allyl pentaerythritol crosslinked), denatured alcohol, ethylhexylglycerin, glycerin, Melaleuca alternafolia (tea tree) leaf oil, organic Ilex paraguariensis (yerba mate) leaf, phenoxyethanol, propylene glycol, triethanolamine, tocopheryl acetate (vitamin E), water

Questions or Comments?

J.R WATKINS, LLC
OAKLAND, CA 94612
1-888-384-1945
JRWATKINS.COM

PRINCIPAL DISPLAY PANEL - 113 g Tube Label

EXTRA STRENGTH*

ESTD 1868
J.R.
WATKINS
REMEDIES FOR BODY™

COOLING

PAIN RELIEF
GEL

WITH NATURAL MENTHOL,
ARNICA & VITAMIN E

FAST-ACTING
MENTHOL PAIN RELIEF
FOR BACKACHES,
SORE MUSCLES,
& JOINT PAIN

USED BY
ATHLETES

NO-MESS APPLICATOR

Net wt. 4.0 oz (113 g)